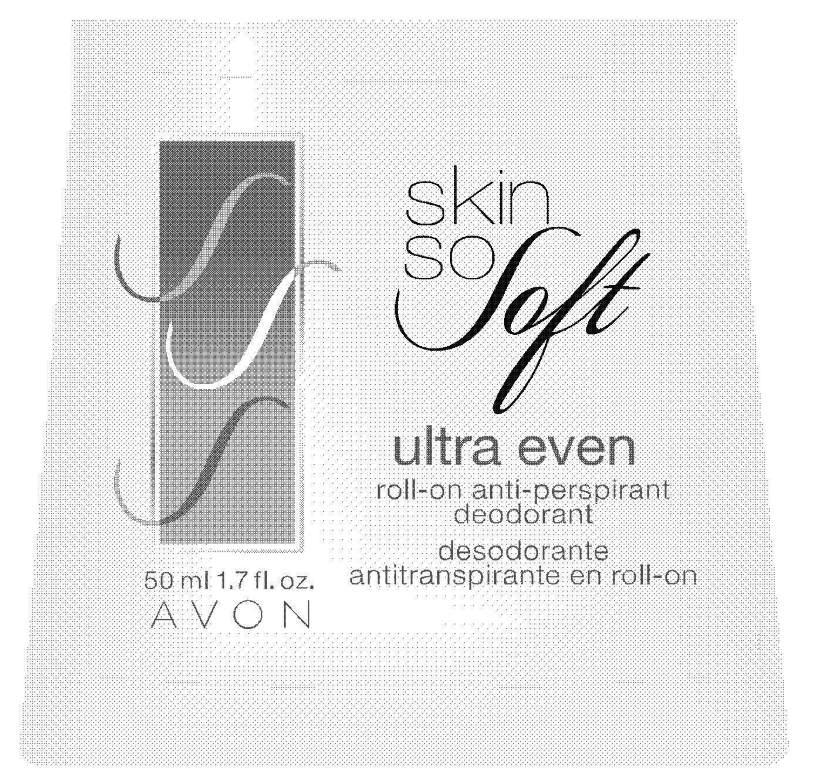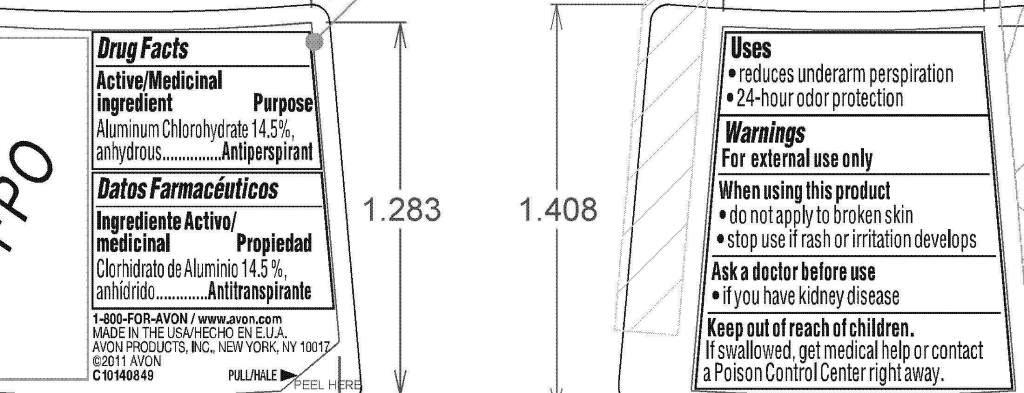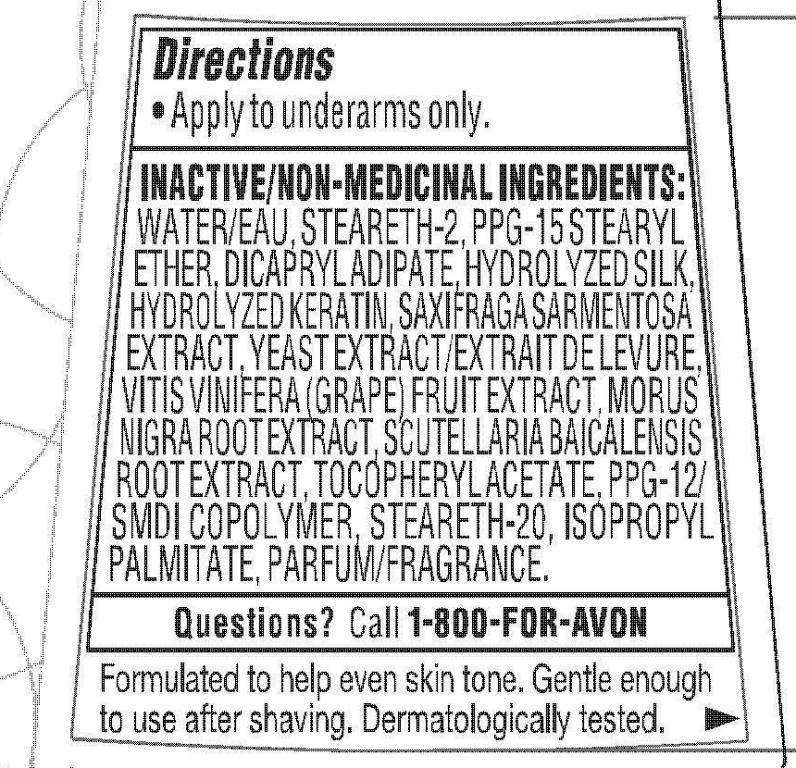 DRUG LABEL: Skin So Soft
NDC: 10096-0246 | Form: GEL
Manufacturer: New Avon LLC
Category: otc | Type: HUMAN OTC DRUG LABEL
Date: 20160217

ACTIVE INGREDIENTS: ALUMINUM CHLOROHYDRATE	 145 mg/1 mL

Active/Medicinal ingredient
Aluminum Chlorohydrate 14.5%, anhydrous............

Purpose.............Antiperspirant

Uses
• reduces underarm perspiration
• 24-hour odor protection

Warnings
For external use only

When using this product
• do not apply to broken skin
• stop use if rash or irritation develops

Ask a doctor before use
• if you have kidney disease

Keep out of reach of children.
If swallowed, get medical help or
contact a Poison Control Center
right away.

Directions
• Apply to underarms only.

INACTIVE/NON-MEDICINAL INGREDIENTS:

WATER/EAU
STEARETH-2
PPG-15 STEARYL ETHER
DICAPRYL ADIPATE
HYDROLYZED SILK
HYDROLYZED KERATIN
SAXIFRAGA SARMENTOSA EXTRACT
YEAST EXTRACT/EXTRAIT DE LEVURE
VITIS VINIFERA (GRAPE) FRUIT EXTRACT
MORUS NIGRA ROOT EXTRACT
SCUTELLARIA BAICALENSIS ROOT EXTRACT
TOCOPHERYL ACETATE
PPG-12/SMDI COPOLYMER
STEARETH-20
ISOPROPYL PALMITATE
PARFUM/FRAGRANCE

Questions? Call 1-800-FOR-AVON